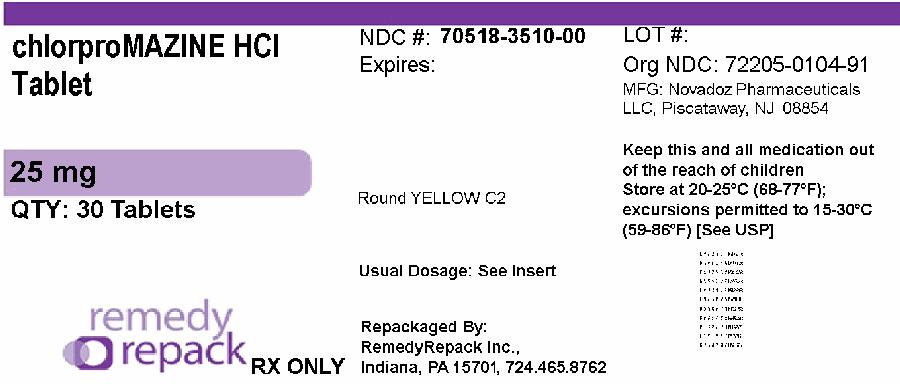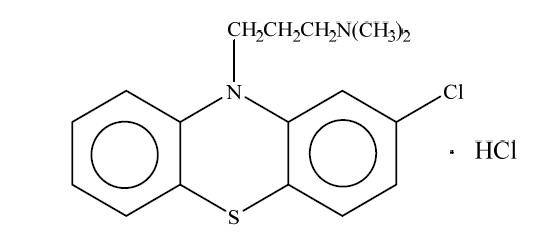 DRUG LABEL: Chlorpromazine Hydrochloride
NDC: 70518-3510 | Form: TABLET, SUGAR COATED
Manufacturer: REMEDYREPACK INC.
Category: prescription | Type: HUMAN PRESCRIPTION DRUG LABEL
Date: 20260302

ACTIVE INGREDIENTS: CHLORPROMAZINE HYDROCHLORIDE 25 mg/1 1
INACTIVE INGREDIENTS: LACTOSE MONOHYDRATE; CROSCARMELLOSE SODIUM; POVIDONE; FERRIC OXIDE YELLOW; MAGNESIUM STEARATE; CALCIUM CARBONATE; SUCROSE; TALC; HYPROMELLOSES; POLYETHYLENE GLYCOL 3350; GLYCERYL MONOSTEARATE; MEDIUM-CHAIN TRIGLYCERIDES; TITANIUM DIOXIDE; FERRIC OXIDE RED; POLYSORBATE 80; SHELLAC; FERROSOFERRIC OXIDE; PROPYLENE GLYCOL

Chlorpromazine Hydrochloride Tablets, USP

WARNING

Increased Mortality in Elderly Patients with Dementia-Related Psychosis
Elderly patients with dementia-related psychosis treated with antipsychotic drugs are at an increased risk of death. Analyses of seventeen placebo-controlled trials (modal duration of 10 weeks), largely in patients taking atypical antipsychotic drugs, revealed a risk of death in drug-treated patients of between 1.6 to 1.7 times the risk of death in placebo-treated patients. Over the course of a typical 10-week controlled trial, the rate of death in drug-treated patients was about 4.5%, compared to a rate of about 2.6% in the placebo group. Although the causes of death were varied, most of the deaths appeared to be either cardiovascular (e.g., heart failure, sudden death) or infectious (e.g., pneumonia) in nature. Observational studies suggest that, similar to atypical antipsychotic drugs, treatment with conventional antipsychotic drugs may increase mortality. The extent to which the findings of increased mortality in observational studies may be attributed to the antipsychotic drug as opposed to some characteristic(s) of the patients is not clear. Chlorpromazine hydrochloride is not approved for the treatment of patients with dementia-related psychosis (see WARNINGS).

DESCRIPTION

Chlorpromazine hydrochloride, USP a dimethylamine derivative of phenothiazine, has a chemical formula of 2-chloro-10-[3-(dimethylamino) propyl] phenothiazine monohydrochloride. Its molecular formula is C17H19ClN2S.HCL and its molecular weight is 355.33. It is available in tablets for oral administration. It has the following structural formula:

Chlorpromazine hydrochloride occurs as white to off-white powder.
Each tablet for oral administration contains 25 mg, 50 mg, 100 mg, or 200 mg of chlorpromazine HCl, USP.
Inactive Ingredients: croscarmellose sodium, glyceryl monostreate, hypromellose, iron oxide yellow, iron oxide red, isopropyl alcohol, lactose monohydrate, magnesium sterate, medium chain triglycerides, polyethylene glycol, polysorbate 80, polyvinyl alcohol, povidone, precipitated calcium carbonate, sucrose, talc, titanium dioxide.
The printing ink contains shellac, ferrosoferric oxide, propylene glycol.

CLINICAL PHARMACOLOGY

The precise mechanism whereby the therapeutic effects of chlorpromazine are produced is not known. The principal pharmacological actions are psychotropic. It also exerts sedative and antiemetic activity. Chlorpromazine has actions at all levels of the central nervous system– primarily at subcortical levels–as well as on multiple organ systems. Chlorpromazine has strong antiadrenergic and weaker peripheral anticholinergic activity; ganglionic blocking action is relatively slight. It also possesses slight antihistaminic and antiserotonin activity.

INDICATIONS AND USAGE

For the management of manifestations of psychotic disorders.
For the treatment of schizophrenia.
To control nausea and vomiting.
For relief of restlessness and apprehension before surgery.
For acute intermittent porphyria.
As an adjunct in the treatment of tetanus.
To control the manifestations of the manic type of manic-depressive illness.
For relief of intractable hiccups.
For the treatment of severe behavioral problems in children (1 to 12 years of age) marked by combativeness and/or explosive hyperexcitable behavior (out of proportion to immediate provocations), and in the short-term treatment of hyperactive children who show excessive motor activity with accompanying conduct disorders consisting of some or all of the following symptoms: impulsivity, difficulty sustaining attention, aggressivity, mood lability and poor frustration tolerance.

CONTRAINDICATIONS

Do not use in patients with known hypersensitivity to phenothiazines.
Do not use in comatose states or in the presence of large amounts of central nervous system depressants (alcohol, barbiturates, narcotics, etc.).

WARNINGS

Increased Mortality in Elderly Patients with Dementia-Related Psychosis
Elderly patients with dementia-related psychosis treated with antipsychotic drugs are at an increased risk of death. Chlorpromazine hydrochloride is not approved for the treatment of patients with dementia-related psychosis (see BOXED WARNING).
The extrapyramidal symptoms which can occur secondary to chlorpromazine may be confused with the central nervous system signs of an undiagnosed primary disease responsible for the vomiting, e.g., Reye's syndrome or other encephalopathy. The use of chlorpromazine and other potential hepatotoxins should be avoided in children and adolescents whose signs and symptoms suggest Reye's syndrome.
Tardive Dyskinesia: Tardive dyskinesia, a syndrome consisting of potentially irreversible, involuntary, dyskinetic movements, may develop in patients treated with antipsychotic drugs. Although the prevalence of the syndrome appears to be highest among the elderly, especially elderly women, it is impossible to rely upon prevalence estimates to predict, at the inception of antipsychotic treatment, which patients are likely to develop the syndrome. Whether antipsychotic drug products differ in their potential to cause tardive dyskinesia is unknown.
Both the risk of developing the syndrome and the likelihood that it will become irreversible are believed to increase as the duration of treatment and the total cumulative dose of antipsychotic drugs administered to the patient increase. However, the syndrome can develop, although much less commonly, after relatively brief treatment periods at low doses.
There is no known treatment for established cases of tardive dyskinesia, although the syndrome may remit, partially or completely, if antipsychotic treatment is withdrawn. Antipsychotic treatment itself, however, may suppress (or partially suppress) the signs and symptoms of the syndrome and therapy may possibly mask the underlying disease process. The effect that symptomatic suppression has upon the long-term course of the syndrome is unknown.
Given these considerations, antipsychotics should be prescribed in a manner that is most likely to minimize the occurrence of tardive dyskinesia. Chronic antipsychotic treatment should generally be reserved for patients who suffer from a chronic illness that, 1) is known to respond to antipsychotic drugs, and, 2) for whom alternative, equally effective, but potentially less harmful treatments are not available or appropriate. In patients who do require chronic treatment, the smallest dose and the shortest duration of treatment producing a satisfactory clinical response should be sought. The need for continued treatment should be reassessed periodically.
If signs and symptoms of tardive dyskinesia appear in a patient on antipsychotics, drug discontinuation should be considered. However, some patients may require treatment despite the presence of the syndrome.
For further information about the description of tardive dyskinesia and its clinical detection, please refer to the sections on PRECAUTIONS and ADVERSE REACTIONS.
Neuroleptic Malignant Syndrome (NMS): A potentially fatal symptom complex sometimes referred to as Neuroleptic Malignant Syndrome (NMS) has been reported in association with antipsychotic drugs. Clinical manifestations of NMS are hyperpyrexia, muscle rigidity, altered mental status and evidence of autonomic instability (irregular pulse or blood pressure, tachycardia, diaphoresis, and cardiac dysrhythmias).
The diagnostic evaluation of patients with this syndrome is complicated. In arriving at a diagnosis, it is important to identify cases where the clinical presentation includes both serious medical illness (e.g., pneumonia, systemic infection, etc.) and untreated or inadequately treated extrapyramidal signs and symptoms (EPS). Other important considerations in the differential diagnosis include central anticholinergic toxicity, heat stroke, drug fever and primary central nervous system (CNS) pathology.
The management of NMS should include 1) immediate discontinuation of antipsychotic drugs and other drugs not essential to concurrent therapy, 2) intensive symptomatic treatment and medical monitoring, and 3) treatment of any concomitant serious medical problems for which specific treatments are available. There is no general agreement about specific pharmacological treatment regimens for uncomplicated NMS.
If a patient requires antipsychotic drug treatment after recovery from NMS, the potential reintroduction of drug therapy should be carefully considered. The patient should be carefully monitored, since recurrences of NMS have been reported.
An encephalopathic syndrome (characterized by weakness, lethargy, fever, tremulousness and confusion, extrapyramidal symptoms, leukocytosis, elevated serum enzymes, BUN and FBS) has occurred in a few patients treated with lithium plus an antipsychotic. In some instances, the syndrome was followed by irreversible brain damage. Because of a possible causal relationship between these events and the concomitant administration of lithium and antipsychotics, patients receiving such combined therapy should be monitored closely for early evidence of neurologic toxicity and treatment discontinued promptly if such signs appear. This encephalopathic syndrome may be similar to or the same as neuroleptic malignant syndrome (NMS).
Patients with bone marrow depression or who have previously demonstrated a hypersensitivity reaction (e.g., blood dyscrasias, jaundice) with a phenothiazine, should not receive any phenothiazine, including chlorpromazine, unless in the judgment of the physician the potential benefits of treatment outweigh the possible hazard.
Chlorpromazine may impair mental and/or physical abilities, especially during the first few days of therapy. Therefore, caution patients about activities requiring alertness (e.g., operating vehicles or machinery).
The use of alcohol with this drug should be avoided due to possible additive effects and hypotension.
Chlorpromazine may counteract the antihypertensive effect of guanethidine and related compounds.
Falls
Chlorpromazine may cause somnolence, postural hypotension, motor and sensory instability, which may lead to falls and, consequently, fractures or other injuries. For patients with diseases, conditions, or medications that could exacerbate these effects, complete fall risk assessments when initiating antipsychotic treatment and recurrently for patients on long-term antipsychotic therapy.
Usage in Pregnancy: Safety for the use of chlorpromazine during pregnancy has not been established. Therefore, it is not recommended that the drug be given to pregnant patients except when, in the judgment of the physician, it is essential. The potential benefits should clearly outweigh possible hazards. There are reported instances of prolonged jaundice, extrapyramidal signs, hyperreflexia or hyporeflexia in newborn infants whose mothers received phenothiazines.
Reproductive studies in rodents have demonstrated potential for embryotoxicity, increased neonatal mortality and nursing transfer of the drug. Tests in the offspring of the drug–treated rodents demonstrate decreased performance. The possibility of permanent neurological damage cannot be excluded.
Non-teratogenic Effects: Neonates exposed to antipsychotic drugs, during the third trimester of pregnancy are at risk for extrapyramidal and/or withdrawal symptoms following delivery. There have been reports of agitation, hypertonia, hypotonia, tremor, somnolence, respiratory distress and feeding disorder in these neonates. These complications have varied in severity; while in some cases symptoms have been self-limited, in other cases neonates have required intensive care unit support and prolonged hospitalization.
Chlorpromazine Hydrochloride should be used during pregnancy only if the potential benefit justifies the potential risk to the fetus.
Nursing Mothers: There is evidence that chlorpromazine is excreted in the breast milk of nursing mothers. Because of the potential for serious adverse reactions in nursing infants from chlorpromazine, a decision should be made whether to discontinue nursing or to discontinue the drug, taking into account the importance of the drug to the mother.

PRECAUTIONS

Leukopenia, Neutropenia and Agranulocytosis
In clinical trial and postmarketing experience, events of leukopenia/neutropenia and agranulocytosis have been reported temporally related to antipsychotic agents.
Possible risk factors for leukopenia/neutropenia include preexisting low white blood cell count (WBC) and history of drug induced leukopenia/neutropenia. Patients with a preexisting low WBC or a history of drug induced leukopenia/neutropenia should have their complete blood count (CBC) monitored frequently during the first few months of therapy and should discontinue Chlorpromazine Hydrochloride Tablets, USP at the first sign of a decline in WBC in the absence of other causative factors.
Patients with neutropenia should be carefully monitored for fever or other symptoms or signs of infection and treated promptly if such symptoms or signs occur. Patients with severe neutropenia (absolute neutrophil count <1000/mm^3) should discontinue Chlorpromazine Hydrochloride Tablets, USP and have their WBC followed until recovery.

General

Given the likelihood that some patients exposed chronically to antipsychotics will develop tardive dyskinesia, it is advised that all patients in whom chronic use is contemplated be given, if possible, full information about this risk. The decision to inform patients and/or their guardians must obviously take into account the clinical circumstances and the competency of the patient to understand the information provided.
Chlorpromazine should be administered cautiously to persons with cardiovascular, liver or renal disease. There is evidence that patients with a history of hepatic encephalopathy due to cirrhosis have increased sensitivity to the CNS effects of chlorpromazine (i.e., impaired cerebration and abnormal slowing of the EEG).
Because of its CNS depressant effect, chlorpromazine should be used with caution in patients with chronic respiratory disorders such as severe asthma, emphysema and acute respiratory infections, particularly in children (1 to 12 years of age).
Because chlorpromazine can suppress the cough reflex, aspiration of vomitus is possible.
Chlorpromazine prolongs and intensifies the action of CNS depressants such as anesthetics, barbiturates and narcotics. When chlorpromazine is administered concomitantly, about ¼ to ½ the usual dosage of such agents is required. When chlorpromazine is not being administered to reduce requirements of CNS depressants, it is best to stop such depressants before starting chlorpromazine treatment. These agents may subsequently be reinstated at low doses and increased as needed.
Note: Chlorpromazine does not intensify the anticonvulsant action of barbiturates. Therefore, dosage of anticonvulsants, including barbiturates, should not be reduced if chlorpromazine is started. Instead, start chlorpromazine at low doses and increase as needed.
Use with caution in persons who will be exposed to extreme heat, organophosphorus insecticides, and in persons receiving atropine or related drugs.
Antipsychotic drugs elevate prolactin levels; the elevation persists during chronic administration. Tissue culture experiments indicate that approximately 1/3 of human breast cancers are prolactindependent in vitro, a factor of potential importance if the prescribing of these drugs is contemplated in a patient with a previously detected breast cancer. Although disturbances such as galactorrhea, amenorrhea, gynecomastia and impotence have been reported, the clinical significance of elevated serum prolactin levels is unknown for most patients. An increase in mammary neoplasms has been found in rodents after chronic administration of antipsychotic drugs. Neither clinical nor epidemiologic studies conducted to date, however, have shown an association between chronic administration of these drugs and mammary tumorigenesis; the available evidence is considered too limited to be conclusive at this time.
Chromosomal aberrations in spermatocytes and abnormal sperm have been demonstrated in rodents treated with certain neuroleptics.
As with all drugs which exert an anticholinergic effect, and/or cause mydriasis, chlorpromazine should be used with caution in patients with glaucoma.
Chlorpromazine diminishes the effect of oral anticoagulants.
Phenothiazines can produce alpha-adrenergic blockade.

Chlorpromazine may lower the convulsive threshold; dosage adjustments of anticonvulsants may be necessary. Potentiation of anticonvulsant effects does not occur. However, it has been reported that chlorpromazine may interfere with the metabolism of phenytoin and thus precipitate phenytoin toxicity.
Concomitant administration with propranolol results in increased plasma levels of both drugs.
Thiazide diuretics may accentuate the orthostatic hypotension that may occur with phenothiazines.
The presence of phenothiazines may produce false-positive phenylketonuria (PKU) test results.
Drugs which lower the seizure threshold, including phenothiazine derivatives, should not be used with metrizamide. As with other phenothiazine derivatives, chlorpromazine should be discontinued at least 48 hours before myelography, should not be resumed for at least 24 hours post-procedure, and should not be used for the control of nausea and vomiting occurring either prior to myelography or post-procedure with metrizamide.
Long-Term Therapy: To lessen the likelihood of adverse reactions related to cumulative drug effect, patients with a history of long-term therapy with chlorpromazine and/or other antipsychotics should be evaluated periodically to decide whether the maintenance dosage could be lowered or drug therapy discontinued.
Antiemetic Effect: The antiemetic action of chlorpromazine may mask the signs and symptoms of overdosage of other drugs and may obscure the diagnosis and treatment of other conditions such as intestinal obstruction, brain tumor and Reye's syndrome. (See WARNINGS).
When chlorpromazine is used with cancer chemotherapeutic drugs, vomiting as a sign of the toxicity of these agents may be obscured by the antiemetic effect of chlorpromazine.
Abrupt Withdrawal: Like other phenothiazines, chlorpromazine is not known to cause psychic dependence and does not produce tolerance or addiction. There may be, however, following abrupt withdrawal of high-dose therapy, some symptoms resembling those of physical dependence such as gastritis, nausea and vomiting, dizziness and tremulousness. These symptoms can usually be avoided or reduced by gradual reduction of the dosage or by continuing concomitant anti-parkinsonism agents for several weeks after chlorpromazine is withdrawn.

ADVERSE REACTIONS

Note: Some adverse effects of chlorpromazine may be more likely to occur, or occur with greater intensity, in patients with special medical problems, e.g., patients with mitral insufficiency or pheochromocytoma have experienced severe hypotension following recommended doses.
Drowsiness: Usually mild to moderate, may occur, particularly during the first or second week, after which it generally disappears. If troublesome, dosage may be lowered.
Jaundice: Overall incidence has been low, regardless of indication or dosage. Most investigators conclude it is a sensitivity reaction. Most cases occur between the second and fourth weeks of therapy. The clinical picture resembles infectious hepatitis, with laboratory features of obstructive jaundice, rather than those of parenchymal damage. It is usually promptly reversible on withdrawal of the medication; however, chronic jaundice has been reported.
There is no conclusive evidence that preexisting liver disease makes patients more susceptible to jaundice. Alcoholics with cirrhosis have been successfully treated with chlorpromazine without complications. Nevertheless, the medication should be used cautiously in patients with liver disease.
Patients who have experienced jaundice with a phenothiazine should not, if possible, be reexposed to chlorpromazine or other phenothiazines.
If fever with grippe-like symptoms occurs, appropriate liver studies should be conducted. If tests indicate an abnormality, stop treatment.
Liver function tests in jaundice induced by the drug may mimic extrahepatic obstruction; withhold exploratory laparotomy until extrahepatic obstruction is confirmed.
Hematological Disorders: including agranulocytosis, eosinophilia, leukopenia, hemolytic anemia, aplastic anemia, thrombocytopenic purpura and pancytopenia have been reported.
Agranulocytosis– Warn patients to report the sudden appearance of sore throat or other signs of infection. If white blood cell and differential counts indicate cellular depression, stop treatment and start antibiotic and other suitable therapy.
Most cases have occurred between the fourth and tenth weeks of therapy; patients should be watched closely during that period.
Moderate suppression of white blood cells is not an indication for stopping treatment unless accompanied by the symptoms described above.
Cardiovascular:
Hypotensive Effects– Postural hypotension, simple tachycardia, momentary fainting and dizziness may occur rarely, after the first oral dose. Usually recovery is spontaneous and symptoms disappear within ½ to 2 hours. Occasionally, these effects may be more severe and prolonged, producing a shock-like condition.
To control hypotension, place patient in head–low position with legs raised. If a vasoconstrictor is required, norepinephrine and phenylephrine are the most suitable. Other pressor agents, including epinephrine, should not be used as they may cause a paradoxical further lowering of blood pressure.

EKG Changes – particularly nonspecific, usually reversible Q and T wave distortions - have been
observed in some patients receiving phenothiazine tranquilizers, including chlorpromazine.
Note: Sudden death, apparently due to cardiac arrest, has been reported.
CNS Reactions:
Extrapyramidal Symptoms– Neuromuscular reactions include dystonias, motor restlessness, pseudo-parkinsonism and tardive dyskinesia, and appear to be dose-related. They are discussed in the following paragraphs:
Dystonia:
Class effect: Symptoms of dystonia, prolonged abnormal contractions of muscle groups, may occur in susceptible individuals during the first few days of treatment. Dystonic symptoms include: spasm of the neck muscles, sometimes progressing to tightness of the throat, swallowing difficulty, difficulty breathing, and/or protrusion of the tongue. While these symptoms can occur at low doses, they occur more frequently and with greater severity with high potency and at higher doses of first generation antipsychotic drugs. An elevated risk of acute dystonia is observed in males and younger age groups.
Motor Restlessness: Symptoms may include agitation or jitteriness and sometimes insomnia. These symptoms often disappear spontaneously. At times these symptoms may be similar to the original neurotic or psychotic symptoms. Dosage should not be increased until these side effects have subsided.
If these symptoms become too troublesome, they can usually be controlled by a reduction of dosage or change of drug. Treatment with anti–parkinsonian agents, benzodiazepines or propranolol may be helpful.
Pseudo – parkinsonism: Symptoms may include: mask-like facies, drooling, tremors, pillrolling motion, cogwheel rigidity and shuffling gait. In most cases these symptoms are readily controlled when an anti–parkinsonism agent is administered concomitantly. Anti–parkinsonism agents should be used only when required. Generally, therapy of a few weeks to 2 or 3 months will suffice. After this time patients should be evaluated to determine their need for continued treatment. (Note: Levodopa has not been found effective in antipsychotic–induced pseudo–parkinsonism.) Occasionally, it is necessary to lower the dosage of chlorpromazine or to discontinue the drug.
Tardive Dyskinesia: As with all antipsychotic agents, tardive dyskinesia may appear in some patients on long-term therapy or may appear after drug therapy has been discontinued. The syndrome can also develop, although much less frequently, after relatively brief treatment periods at low doses. This syndrome appears in all age groups. Although its prevalence appears to be highest among elderly patients, especially elderly women, it is impossible to rely upon prevalence estimates to predict at the inception of antipsychotic treatment which patients are likely to develop the syndrome. The symptoms are persistent and in some patients appear to be irreversible. The syndrome is characterized by rhythmical involuntary movements of the tongue, face, mouth or jaw (e.g., protrusion of tongue, puffing of cheeks, puckering of mouth, chewing movements). Sometimes these may be accompanied by involuntary movements of extremities. In rare instances, these involuntary movements of the extremities are the only manifestations of tardive dyskinesia. A variant of tardive dyskinesia, tardive dystonia, has also been described.
There is no known effective treatment for tardive dyskinesia; anti-parkinsonism agents do not alleviate the symptoms of this syndrome. If clinically feasible, it is suggested that all antipsychotic agents be discontinued if these symptoms appear. Should it be necessary to reinstitute treatment, or increase the dosage of the agent, or switch to a different antipsychotic agent, the syndrome may be masked.
It has been reported that fine vermicular movements of the tongue may be an early sign of the syndrome and, if the medication is stopped at that time, the syndrome may not develop.
Adverse Behavioral Effects –Psychotic symptoms and catatonic-like states have been reported rarely.
Other CNS Effects –Neuroleptic Malignant Syndrome (NMS) has been reported in association with antipsychotic drugs. (See WARNINGS.)
Cerebral edema has been reported.
Convulsive seizures (petit mal and grand mal) have been reported, particularly in patients with EEG abnormalities or history of such disorders.
Abnormality of the cerebrospinal fluid proteins has also been reported.
Allergic Reactions of a mild urticarial type of photosensitivity are seen. Avoid undue exposure to sun. More severe reactions, including exfoliative dermatitis and toxic epidermal necrolysis (TEN), have been reported occasionally.
Contact dermatitis has been reported in nursing personnel; accordingly, the use of rubber gloves when administering chlorpromazine liquid or injectable is recommended.
In addition, asthma, laryngeal edema, angioneurotic edema and anaphylactoid reactions have been reported.
Endocrine Disorders: Lactation and moderate breast engorgement may occur in females on large doses. If persistent, lower dosage or withdraw drug. False-positive pregnancy tests have been reported, but are less likely to occur when a serum test is used. Amenorrhea and gynecomastia have also been reported. Hyperglycemia, hypoglycemia and glycosuria have been reported.
Autonomic Reactions: Occasional dry mouth; nasal congestion; nausea; obstipation; constipation; adynamic ileus; urinary retention, priapism; miosis and mydriasis, atonic colon, ejaculatory disorders/impotence.
Special Considerations In Long-Term Therapy: Skin pigmentation and ocular changes have occurred in some patients taking substantial doses of chlorpromazine for prolonged periods.
Skin Pigmentation– Rare instances of skin pigmentation have been observed in hospitalized mental patients, primarily females who have received the drug usually for 3 years or more in dosages ranging from 500 mg to 1,500 mg daily.
The pigmentary changes, restricted to exposed areas of the body, range from an almost imperceptible darkening of the skin to a slate gray color, sometimes with a violet hue. Histological examination reveals a pigment, chiefly in the dermis, which is probably a melanin-like complex. This pigmentation may fade following discontinuance of the drug.
Ocular Changes –Ocular changes have occurred more frequently than skin pigmentation and have been observed both in pigmented and nonpigmented patients receiving chlorpromazine usually for 2 years or more in dosages of 300 mg daily and higher. Eye changes are characterized by deposition of fine particulate matter in the lens and cornea. In more advanced cases, star-shaped opacities have also been observed in the anterior portion of the lens. The nature of the eye deposits has not yet been determined. A small number of patients with more severe ocular changes have had some visual impairment. In addition to these corneal and lenticular changes, epithelial keratopathy and pigmentary retinopathy have been reported. Reports suggest that the eye lesions may regress after withdrawal of the drug.
Since the occurrence of eye changes seems to be related to dosage levels and/or duration of therapy, it is suggested that long-term patients on moderate to high dosage levels have periodic ocular examinations.
Etiology–Etiology of both of these reactions is not clear, but exposure to light, along with dosage/duration of therapy, appears to be the most significant factor. If either of these reactions is observed, the physician should weigh the benefits of continued therapy against the possible risks and, on the merits of the individual case, determine whether or not to continue present therapy, lower the dosage, or withdraw the drug.
Other Adverse Reactions: Mild fever may occur after large I.M. doses. Hyperpyrexia has been reported. Increases in appetite and weight sometimes occur. Peripheral edema and a systemic lupus erythematosus-like syndrome have been reported.
Note: There have been occasional reports of sudden death in patients receiving phenothiazines. In some cases, the cause appeared to be cardiac arrest or asphyxia due to failure of the cough reflex.

OVERDOSAGE

(See also ADVERSE REACTIONS.)
Symptoms
Primarily symptoms of central nervous system depression to the point of somnolence or coma.
Hypotension and extrapyramidal symptoms.
Other possible manifestations include agitation and restlessness, convulsions, fever, autonomic reactions such as dry mouth and ileus. EKG changes and cardiac arrhythmias.
Treatment
It is important to determine other medications taken by the patient since multiple drug therapy is common in overdosage situations. Treatment is essentially symptomatic and supportive. Early gastric lavage is helpful. Keep patient under observation and maintain an open airway, since involvement of the extrapyramidal mechanism may produce dysphagia and respiratory difficulty in severe overdosage. Do not attempt to induce emesis because a dystonic reaction of the head or neck may develop that could result in aspiration of vomitus. Extrapyramidal symptoms may be treated with anti-parkinsonism drugs, barbiturates, or diphenhydramine hydrochloride. See prescribing information for these products. Care should be taken to avoid increasing respiratory depression.
If administration of a stimulant is desirable, amphetamine, dextroamphetamine, or caffeine with sodium benzoate is recommended. Stimulants that may cause convulsions (e.g., picrotoxin or pentylenetetrazol) should be avoided.
If hypotension occurs, the standard measures for managing circulatory shock should be initiated. If it is desirable to administer a vasoconstrictor, norepinephrine and phenylephrine are most suitable. Other pressor agents, including epinephrine, are not recommended because phenothiazine derivatives may reverse the usual elevating action of these agents and cause a further lowering of blood pressure.
Limited experience indicates that phenothiazines are not dialyzable.

DOSAGE AND ADMINISTRATION-ADULTS

Adjust dosage to individual and the severity of his condition, recognizing that the milligram for milligram potency relationship among all dosage forms has not been precisely established clinically. It is important to increase dosage until symptoms are controlled. Dosage should be increased more gradually in debilitated or emaciated patients. In continued therapy, gradually reduce dosage to the lowest effective maintenance level, after symptoms have been controlled for a reasonable period.
The 100 mg and 200 mg tablets are for use in severe neuropsychiatric conditions.
Elderly Patients – In general, dosages in the lower range are sufficient for most elderly patients. Since they appear to be more susceptible to hypotension and neuromuscular reactions, such patients should be observed closely. Dosage should be tailored to the individual, response carefully monitored, and dosage adjusted accordingly. Dosage should be increased more gradually in elderly patients.
Psychotic Disorders – Increase dosage gradually until symptoms are controlled. Maximum mprovement may not be seen for weeks or even months. Continue optimum dosage for 2 weeks; then gradually reduce dosage to the lowest effective maintenance level. Daily dosage of 200 mg is not unusual. Some patients require higher dosages (e.g., 800 mg daily is not uncommon in discharged mental patients).
Hospitalized Patients:
Acute Schizophrenic or Manic States – It is recommended that initial treatment be with chlorpromazine HCI injection until patient is controlled. Usually patient becomes quiet and co-operative within 24 to 48 hours and oral doses may be substituted and increased until the patient is calm. 500 mg a day is generally sufficient. While gradual increases to 2,000 mg a day or more may be necessary, there is usually little therapeutic gain to be achieved by exceeding 1,000 mg a day for extended periods. In general, dosage levels should be lower in the elderly, the emaciated and the debilitated.
Less Acutely Disturbed – 25 mg t.i.d. Increase gradually until effective dose is reached – usually 400 mg daily.
Outpatients – 10 mg t.i.d. or q.i.d., or 25 mg b.i.d. or t.i.d.
More Severe Cases – 25 mg t.i.d. After 1 or 2 days, daily dosage may be increased by 20 to 50 mg at semi-weekly intervals until patient becomes calm and cooperative.
Prompt Control of Severe Symptoms – Initial treatment should be with intramuscular chlorpromazine. Subsequent doses should be oral, 25 to 50 mg t.i.d.
Nausea and Vomiting– 10 to 25 mg q4 to 6h, p.r.n., increased, if necessary.
Presurgical Apprehension– 25 to 50 mg, 2 to 3 hours before the operation.
Intractable Hiccups– 25 to 50 mg t.i.d. or q.i.d. If symptoms persist for 2 to 3 days, parenteral therapy is indicated.
Acute Intermittent Porphyria– 25 to 50 mg t.i.d. or q.i.d. Can usually be discontinued after several weeks, but maintenance therapy may be necessary for some patients.

HOW SUPPLIED

Chlorpromazine HCl Tablets, USP, 25 mg are light yellow to yellow colored, round shaped, biconvex, sugar coated tablets, imprinted "C2" with black ink on one side and plain on other side.

NDC: 70518-3510-00

NDC: 70518-3510-01

NDC: 70518-3510-02

PACKAGING: 30 in 1 BLISTER PACK

PACKAGING: 100 in 1 BOX

PACKAGING: 1 in 1 POUCH

Store at 20° to 25°C (68° to 77°F); excursions permitted between 15° to 30°C (59° to 86°F) [See USP Controlled Room Temperature.] Protect from light and moisture.

This package is not for household dispensing. If dispensed for outpatient use, a well closed, light-resistant, child-resistant container should be utilized.

Keep out of reach of children.

Rx only

Repackaged and Distributed By:

Remedy Repack, Inc.

625 Kolter Dr. Suite #4 Indiana, PA 1-724-465-8762

DOSAGE AND ADMINISTRATION – PEDIATRIC PATIENTS (6 months to 12 years of age)

Chlorpromazine should generally not be used in pediatric patients under 6 months of age except where potentially lifesaving. It should not be used in conditions for which specific pediatric dosages have not been established.
Severe Behavioral Problems
Outpatients – Select route of administration according to severity of patient's condition and increase dosage gradually as required. Oral: ¼ mg/lb body weight q4 to 6h, p.r.n. (e.g., for 40 lb child –10 mg q4 to 6h).
Hospitalized Patients – As with outpatients, start with low doses and increase dosage gradually. In severe behavior disorders higher dosages (50 to 100 mg daily and in older children, 200 mg daily or more) may be necessary. There is little evidence that behavior improvement in severely disturbed mentally retarded patients is further enhanced by doses beyond 500 mg per day.
Nausea and Vomiting– Dosage and frequency of administration should be adjusted according to the severity of the symptoms and response of the patient. The duration of activity following intramuscular administration may last up to 12 hours. Subsequent doses may be given by the same route if necessary. Oral: ¼ mg/lb body weight (e.g., 40 lb child – 10 mg q4 to 6h).
Presurgical Apprehension– ¼ mg/lb body weight orally 2 to 3 hours before operation.

PACKAGE LABEL

DRUG: Chlorpromazine Hydrochloride

GENERIC: Chlorpromazine Hydrochloride

DOSAGE: TABLET, SUGAR COATED

ADMINSTRATION: ORAL

NDC: 70518-3510-0

NDC: 70518-3510-1

NDC: 70518-3510-2

COLOR: yellow

SHAPE: ROUND

SCORE: No score

SIZE: 8 mm

IMPRINT: C2

PACKAGING: 30 in 1 BLISTER PACK

PACKAGING: 100 in 1 BOX

PACKAGING: 1 in 1 POUCH

ACTIVE INGREDIENT(S):

- CHLORPROMAZINE HYDROCHLORIDE 25mg in 1

INACTIVE INGREDIENT(S):

- PROPYLENE GLYCOL
- SHELLAC
- POLYSORBATE 80
- FERRIC OXIDE RED
- TITANIUM DIOXIDE
- MEDIUM-CHAIN TRIGLYCERIDES
- GLYCERYL MONOSTEARATE
- POLYETHYLENE GLYCOL 3350
- LACTOSE MONOHYDRATE
- TALC
- SUCROSE
- CALCIUM CARBONATE
- MAGNESIUM STEARATE
- FERRIC OXIDE YELLOW
- POVIDONE
- CROSCARMELLOSE SODIUM
- FERROSOFERRIC OXIDE
- HYPROMELLOSES